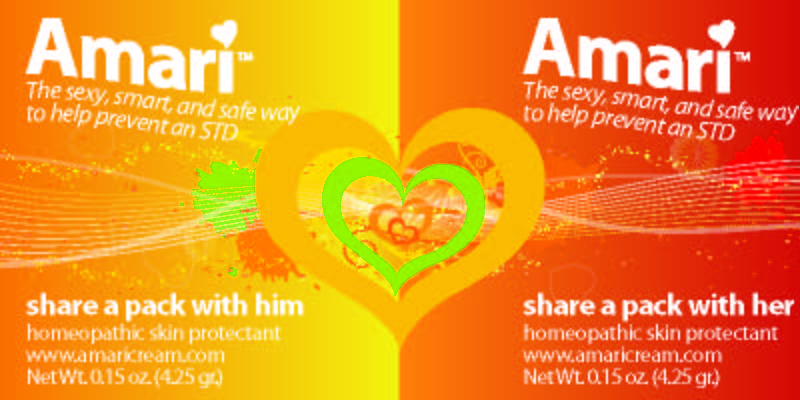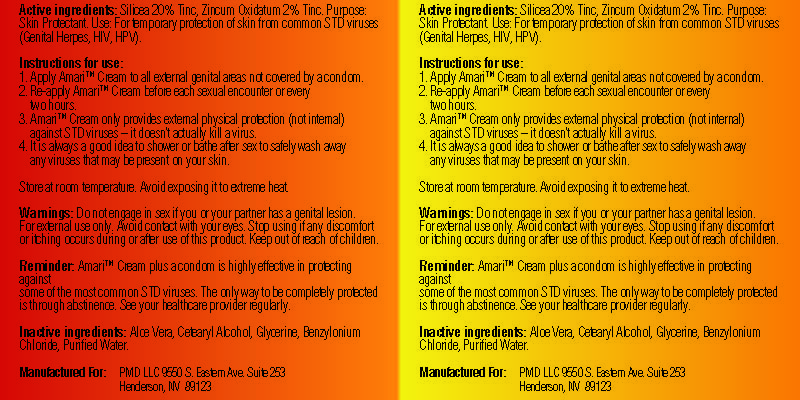 DRUG LABEL: Amari
NDC: 49811-001 | Form: CREAM
Manufacturer: Pacific Media Direct, LLC
Category: homeopathic | Type: HUMAN OTC DRUG LABEL
Date: 20091116

ACTIVE INGREDIENTS: SILICON DIOXIDE .85 g/4.25 g; ZINC OXIDE .085 g/4.25 g

Amari

DESCRIPTION

Instructions for use:

1. Apply Amari Cream to all external genital areas not covered by a condom.

2. Re-apply Amari Cream before each sexual encounter or every two hours.

3. Amari Cream only provides external physical protection (not internal) against STD viruses - it doesn't actually kill a virus.

4. It is always a good idea to shower or bathe after sex to safely wash away any viruses that may present on your skin.

Store at room temperature. Avoid exposing it to extreme heat.

Reminder: Amari Cream plus a condom is highly effective in protecting against some of the most common STD viruses.

The only way to be completely protected is through abstinence. See your healthcare provider regularly.

Manufactured For:PMD LLC 9550 S. Eastern Ave. Suite 253

Henderson, NV 89123

INACTIVE INGREDIENT

Inactive Ingredients: Aloe Vera, Cetearyl Alcohol, Glycerine, Benzylonium Chloride, Purified Water

WARNINGS

Warnings:Do not engage in sex if you or your partner has a genital lesion. For external use only. Avoid contact with your eyes. Stop using if any discomfort or itching occurs during or after use of this product. Keep out of reach of children.

PACKAGE LABEL

Enter section text here